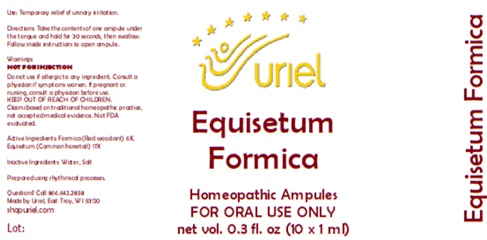 DRUG LABEL: Equisetum Formica
NDC: 48951-4035 | Form: LIQUID
Manufacturer: Uriel Pharmacy Inc.
Category: homeopathic | Type: HUMAN OTC DRUG LABEL
Date: 20260227

ACTIVE INGREDIENTS: FORMICA RUFA 6 [hp_X]/1 mL; EQUISETUM ARVENSE TOP 17 [hp_X]/1 mL
INACTIVE INGREDIENTS: WATER; SODIUM CHLORIDE

Equisetum Formica

PURPOSE

Use: Temporary relief of urinary irritation.

INDICATIONS AND USAGE

FOR ORAL USE ONLY

DOSAGE AND ADMINISTRATION

Directions: Take the contents of one ampule under the tongue and hold for 30 seconds, then swallow. Follow inside instructions to open ampule.

Warnings:
NOT FOR INJECTION
Do not use if allergic to any ingredient. Consult a physician if symptoms worsen. If pregnant or nursing, consult a physician before use.
Claims based on traditional homeopathic practice, not accepted medical evidence. Not FDA evaluated.

KEEP OUT OF REACH OF CHILDREN.

ACTIVE INGREDIENT

Active Ingredients: Formica (Red wood ant) 6X, Equisetum (Common horsetail) 17X

Inactive Ingredients: Water, Salt

Prepared using rhythmical processes.

QUESTIONS

Questions? Call 866.642.2858 Made by Uriel, East Troy, WI 53120 shopuriel.com

Lot: